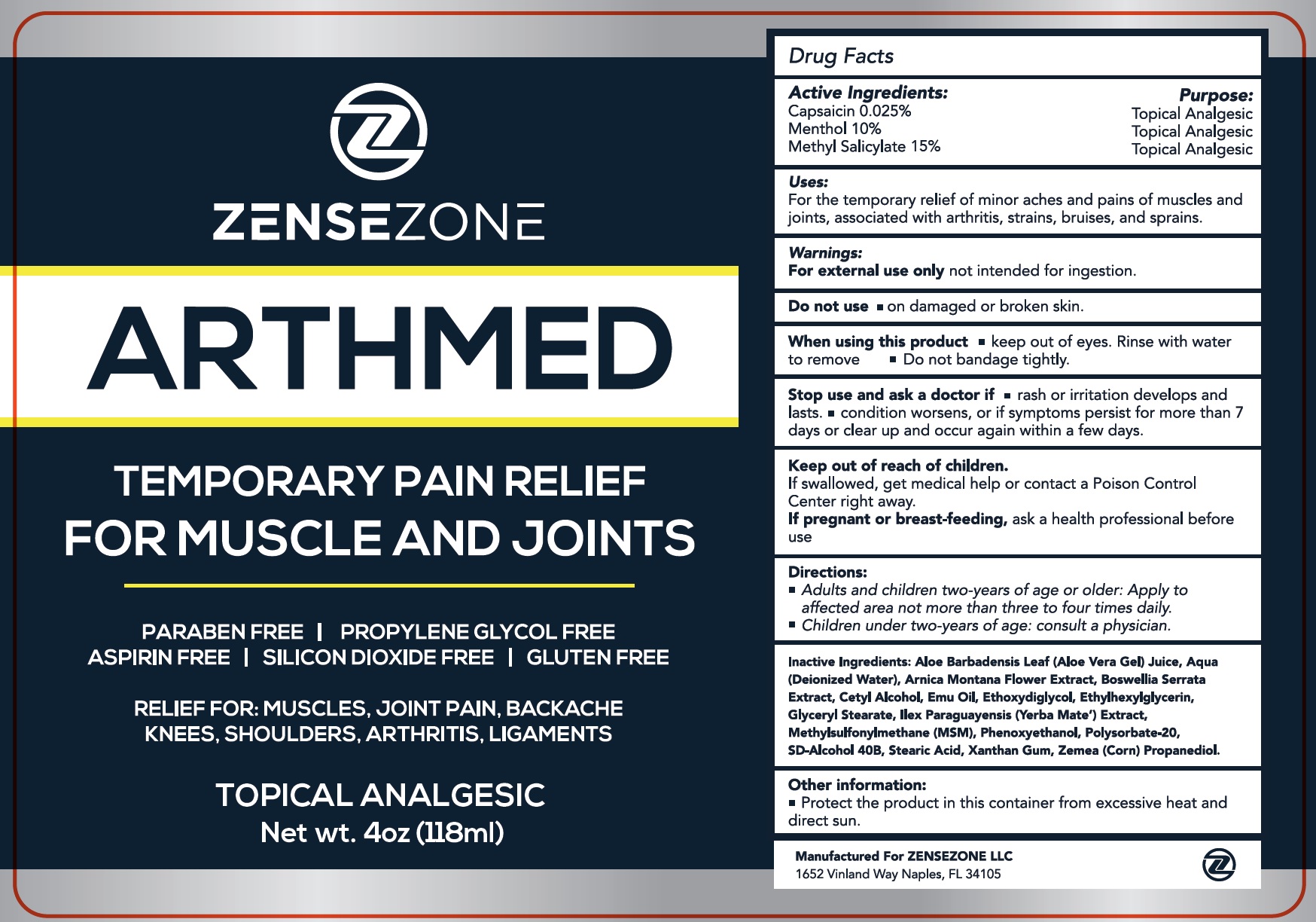 DRUG LABEL: ZENSEZONE Arthmed Temporary Pain Relief Cream
NDC: 82319-240 | Form: CREAM
Manufacturer: ZENSEZONE LLC
Category: otc | Type: HUMAN OTC DRUG LABEL
Date: 20231111

ACTIVE INGREDIENTS: CAPSAICIN 0.25 mg/1 mL; MENTHOL 100 mg/1 mL; METHYL SALICYLATE 150 mg/1 mL
INACTIVE INGREDIENTS: ALOE VERA LEAF; WATER; ARNICA MONTANA FLOWER; INDIAN FRANKINCENSE; CETYL ALCOHOL; EMU OIL; DIETHYLENE GLYCOL MONOETHYL ETHER; ETHYLHEXYLGLYCERIN; GLYCERYL MONOSTEARATE; ILEX PARAGUARIENSIS LEAF; DIMETHYL SULFONE; PHENOXYETHANOL; POLYSORBATE 20; STEARIC ACID; XANTHAN GUM; CORN

ZENSEZONE Arthmed Temporary Pain Relief Cream

Active Ingredients:

Capsaicin 0.025%

Menthol 10%

Methyl Salicylate 15%

Purpose:

Topical Analgesic

Uses:

For the temporary relief of minor aches and pains of muscles and joints, associated with arthritis, strains, bruises, and sprains.

Warnings:

not intended for ingestion. For external use only

Do not use

- on damaged or broken skin.

When using this product

- keep out of eyes. Rinse with water to remove
- Do not bandage tightly.

Stop use and ask a doctor if

- rash or irritation develops and lasts.
- condition worsens, or if symptoms persist for more than 7 days or clear up and occur agin within a few days.

Keep out of reach of children.

If swallowed, get medical help or contact a Poison Control Center right away.

If pregnant or breast-feeding,

ask a health professional before use

Directions:

- Adults and children two-years of age an older: Apply to affected area not more than three to four times daily.
- Children under two-years of age: consult a physician.

Inactive Ingredients:

Aloe Barbadensis Leaf (Aloe Vera Gel) Juice, Aqua (Deionized Water), Arnica Montana Flower Extract, Boswellia Serrata Extract, Cetyl Alcohol, Emu Oil, Ethoxydiglycol, Ethylhexylglycerin, Glyceryl Stearate, Ilex Paraguayensis (Yerba Mate') Extract, Methylsulfonylmethane (MSM), Phenoxyethanol, Polysorbate-20, SD-Alcohol 40B, Stearic Acid, Xanthan Gum, Zemea (Corn) Propanediol.

Other information:

- Potect the product in this container from excessive heat and direct sun.